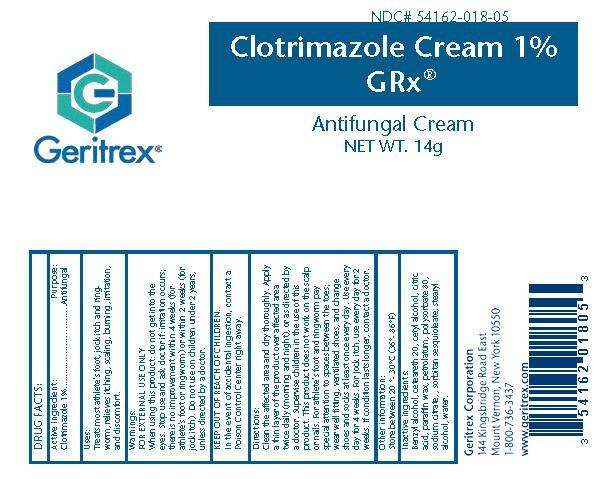 DRUG LABEL: CLOTRIMAZOLE
NDC: 54162-018 | Form: CREAM
Manufacturer: Geritrex Corp
Category: otc | Type: HUMAN OTC DRUG LABEL
Date: 20140729

ACTIVE INGREDIENTS: CLOTRIMAZOLE 1 g/100 g
INACTIVE INGREDIENTS: BENZYL ALCOHOL; CETEARETH-2 PHOSPHATE; CETYL ALCOHOL; CITRIC ACID ACETATE; PARAFFIN; PETROLATUM; POLYSORBATE 80; SODIUM CITRATE; SORBITAN SESQUIOLEATE; STEARYL ALCOHOL; WATER

Clotrimazole Cream 1%

Drug Facts

Active Ingredient: Purpose

Clotrimazole 1% Antifungal

Uses

Treats most athlet's foot, jock itch and ringworm, relieves itching, scaling, burning, irritation, and discomfort

Directions

Clean the affected area and dry thoroughly Apply a thin layer of the product over affected area twice daily(morning and night), or as directed by a doctor Supervise children in the use of this products.This products does not work on the scalp or nail. For athlet's foot and ringworm pay special attention to spaces between the toes: wear well fitting, ventilates shoes, and change shoes and socks at least once every day. Use every day for 4 weeks. For jock itch, use every day for 2 weeks. If condition lasts longer, contact a doctor.

Warnings

FOR EXTERNAL USE ONLY

When using this product do not get in to the eyes. Stop use and ask doctor if irritation occurs there is no improvement within 4 weeks (for athlet's foot or ringworm) or within 2 weeks (for jock itch). Do not use on children under 2 years, unless directed by a doctor.

Inactive Ingredients

Benzyl alcohol, Cetearth 20, Cetyl alcohol, Citric acid, Paraffin wax, Petrolatum, Polysorbate 80, Sodium citrate, Sorbitan sesquioleate, Stearyl alcohol, Water

KEEP OUT OF REACH OF CHILDREN

In the event of accidental ingestion, contact a Poison Control Center right away.

STORAGE AND HANDLING

Store between 20'-30'C (36'-86'F)

DOSAGE AND ADMINISTRATION

Use every day for 4 weeks. For jock itch, use every day for 2 weeks. if conditon lasts longer, contact a doctor